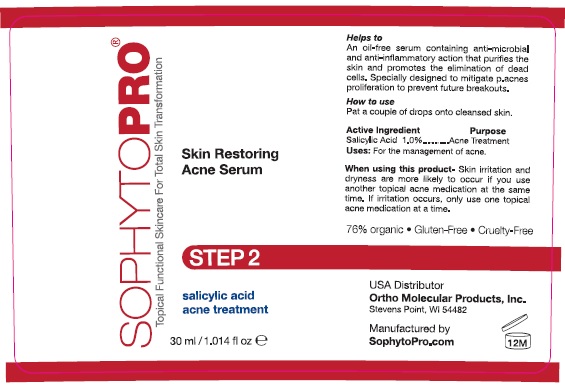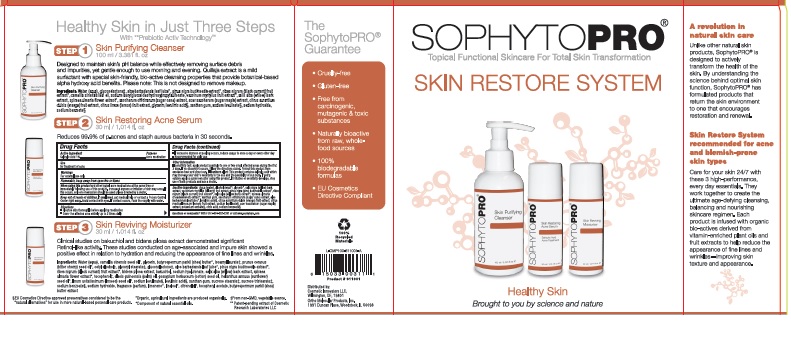 DRUG LABEL: Acne Serum
NDC: 61531-101 | Form: GEL
Manufacturer: Universal Packaging Systems, Inc.  DBA: Paklab
Category: otc | Type: HUMAN OTC DRUG LABEL
Date: 20151026

ACTIVE INGREDIENTS: SALICYLIC ACID 0.01 g/1 g
INACTIVE INGREDIENTS: GLYCERIN

ACTIVE INGREDIENT

Salicylic Acid 1.0%

PURPOSE

Acne medication

INDICATIONS AND USAGE

for treatment of acne

WARNINGS

For external use only

WARNINGS AND PRECAUTIONS

Flammable, keep away from open fire or flame

When using this product and other topical acne medications at the same time or immediately following use of this product, increased dryness of irritation of skin may occur. If this occurs, only one medication should be used unless directed by a doctor

KEEP OUT OF REACH OF CHILDREN

If swallowed, get medical help or contact a Poison Control Center right away. Avoid contact with eyes. If contact occurs, flush thoroughly with water.

INSTRUCTIONS FOR USE

- Cleanse skin thoroughly before applying medication
- Cover the affected area entirely up to 2 times daily
- If excessinve dryness or peeling occurs, reduce usage to once a day or every other day
- Recommended for daily use

INACTIVE INGREDIENT

Water (Aqua), Alcohol Denat., Glycerin, Salix Nigra (Willow) Bark Extract,Vaccinium Myrtillus Fruit Extract,

Pinus Nigra Bud/Needle Extract, Ribes Nigrum (Black Currant) Fruit Extract, Xanthan Gum, Saccharum Officinarum (Sugar Cane) Extract, Salix Alba (Willow) Bark Extract, Spiraea Ulmaria Flower Extract, Levulinic Acid, Aloe Barbadensis Leaf Juice, Citrus Aurantium Dulcis (Orange) Fruit Extract, Citrus Limon (Lemon) Fruit Extract, Sodium Levulinate, Citric Acid, Acer Saccharum (Sugar Maple) Extract

DOSAGE AND ADMINISTRATION

Topical gel